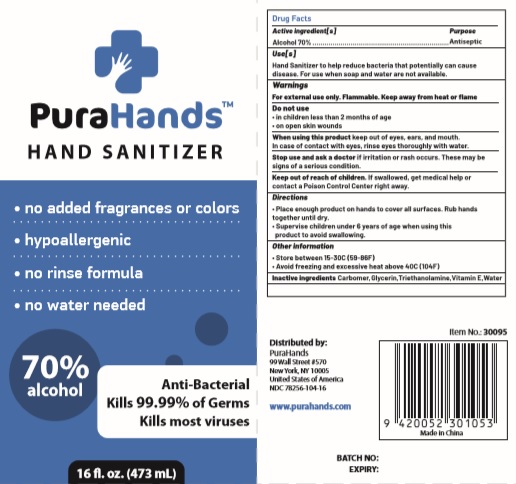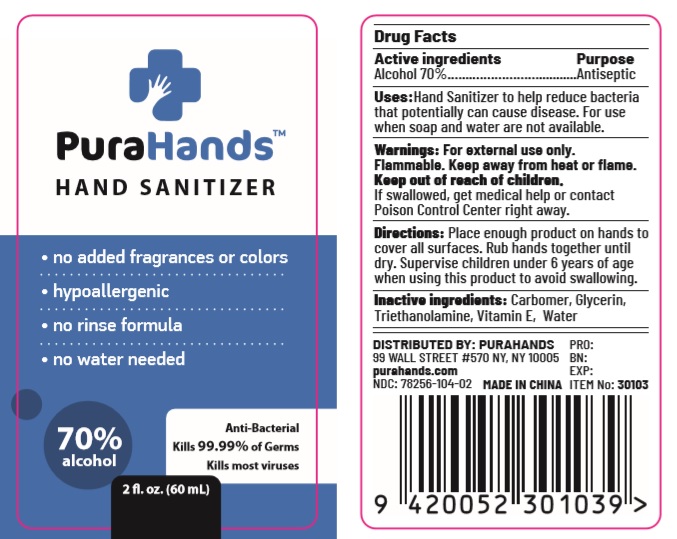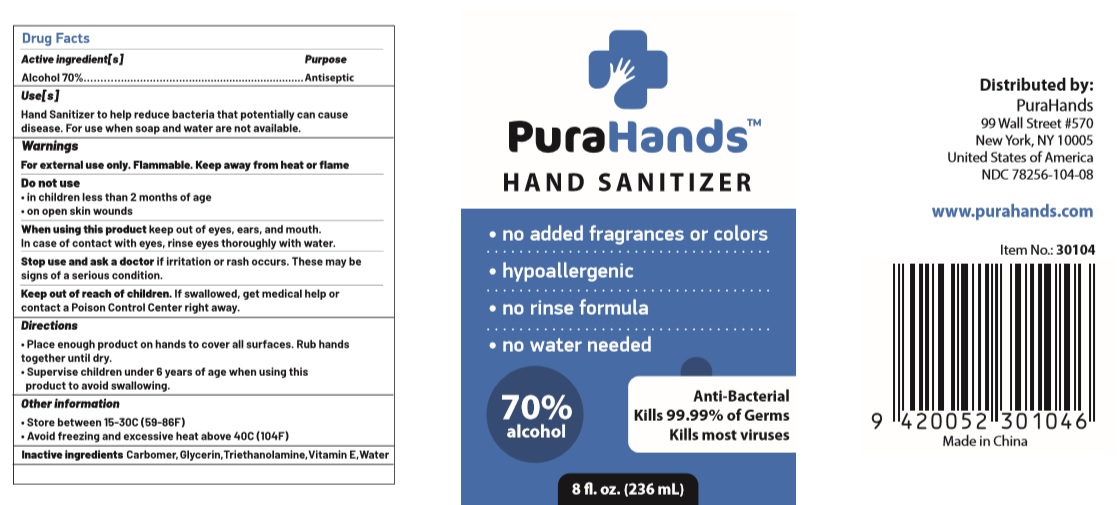 DRUG LABEL: PuraHands Hand Sanitizer
NDC: 78256-104 | Form: GEL
Manufacturer: Etailer Limited
Category: otc | Type: HUMAN OTC DRUG LABEL
Date: 20200611

ACTIVE INGREDIENTS: ALCOHOL 70 mL/100 mL
INACTIVE INGREDIENTS: TROLAMINE; CARBOMER HOMOPOLYMER, UNSPECIFIED TYPE; GLYCERIN; .ALPHA.-TOCOPHEROL; WATER

PuraHands Hand Sanitizer (gel - 2 fl oz.) NDC: 78256-104-02;
PuraHands Hand Sanitizer (gel - 8 fl oz.) NDC: 78256-104-08;
PuraHands Hand Sanitizer (gel - 16 fl oz.) NDC: 78256-104-16

Active Ingredient(s)

Alcohol 70% v/v.

Purpose

Antiseptic

Use

Hand Sanitizer to help reduce bacteria that potentially can cause disease. For use when soap and water are not available.

Warnings

For external use only. Flammable. Keep away from heat or flame

Do not use

- in children less than 2 months of age
- on open skin wounds

When using this product keep out of eyes, ears, and mouth. In case of contact with eyes, rinse eyes thoroughly with water.

Stop use and ask a doctor if irritation or rash occurs. These may be signs of a serious condition.

Keep out of reach of children. If swallowed, get medical help or contact a Poison Control Center right away.

Directions

- Place enough product on hands to cover all surfaces. Rub hands together until dry.
- Supervise children under 6 years of age when using this product to avoid swallowing.

Other information

- Store between 15-30C (59-86F)
- Avoid freezing and excessive heat above 40C (104F)

Inactive ingredients

Carbomer, Glycerin, Triethanolamine, Vitamin E, Water

Package Label - Principal Display Panel

DISTRIBUTED BY:

PuraHands

99 Wall Street #570

New York, NY 10005

PuraHands Hand Sanitizer (2 fl. oz.) NDC: 78256-104-02

PuraHands Hand Sanitizer (8 fl. oz.) NDC: 78256-104-08

PuraHands Hand Sanitizer (16 fl. oz.) NDC: 78256-104-16